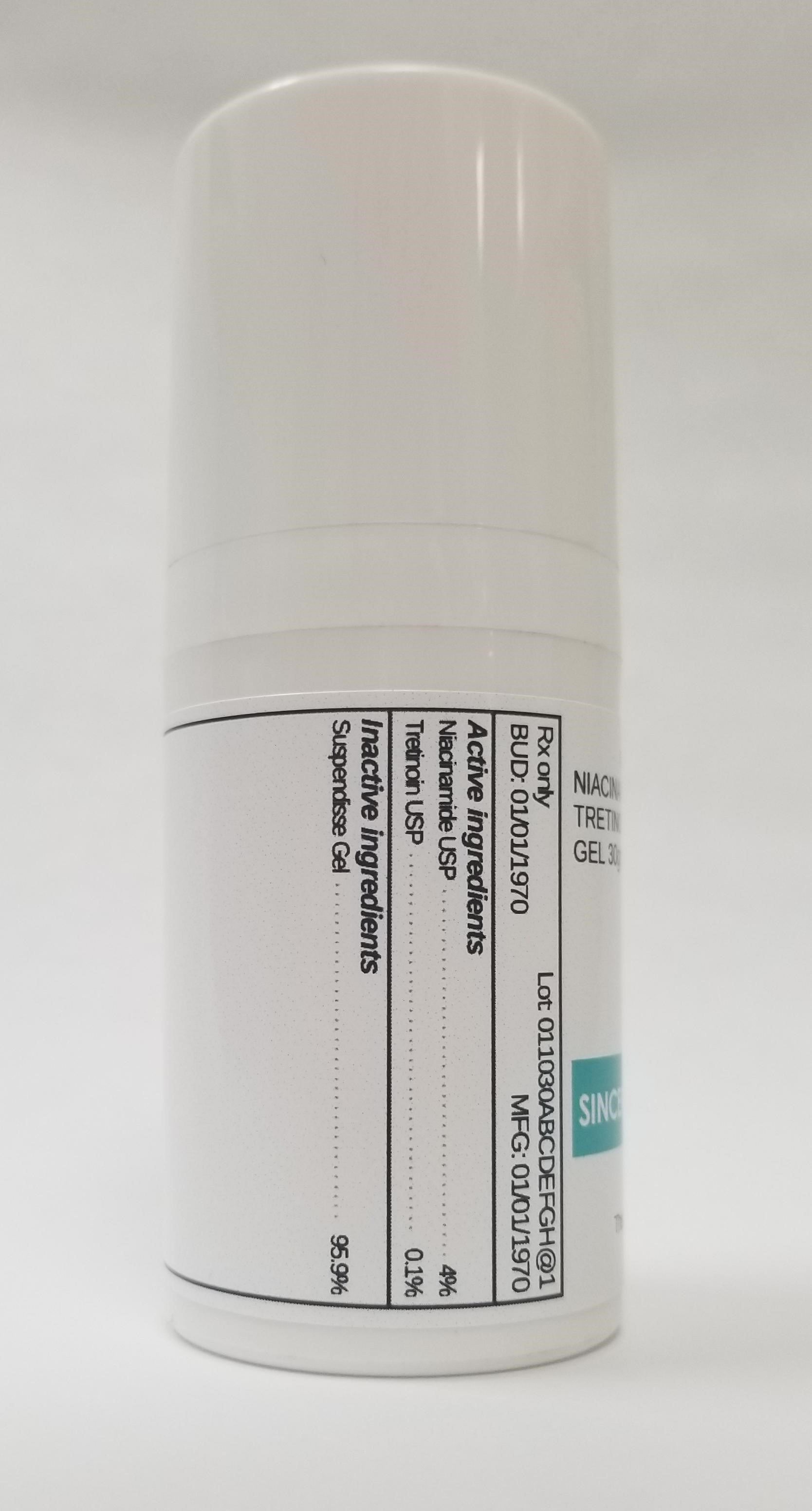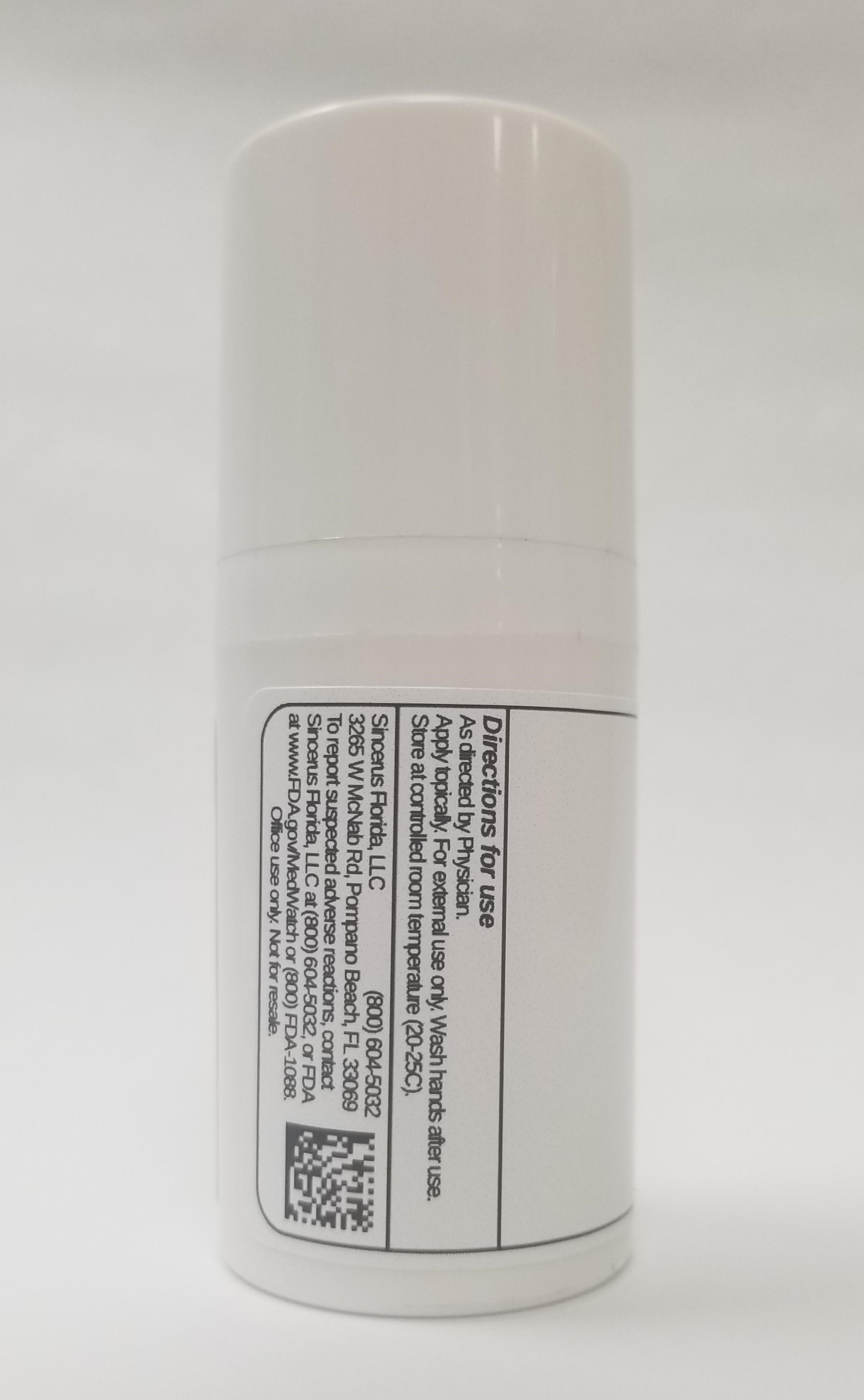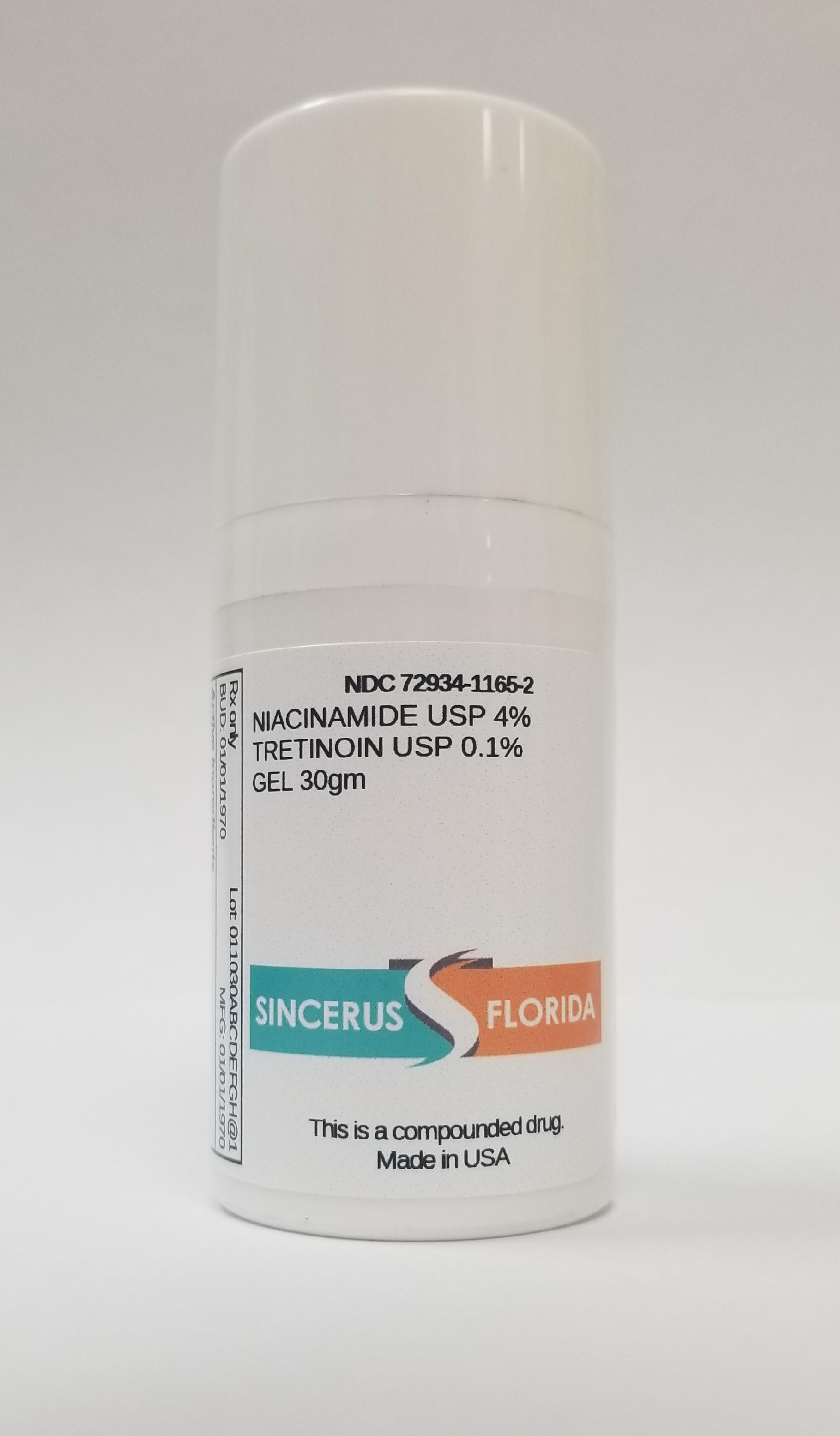 DRUG LABEL: NIACINAMIDE 4% / TRETINOIN 0.1%
NDC: 72934-1165 | Form: GEL
Manufacturer: Sincerus Florida, LLC
Category: prescription | Type: HUMAN PRESCRIPTION DRUG LABEL
Date: 20190329

ACTIVE INGREDIENTS: TRETINOIN 0.1 g/100 g; NIACINAMIDE 4 g/100 g

NIACINAMIDE 4% / TRETINOIN 0.1% GEL